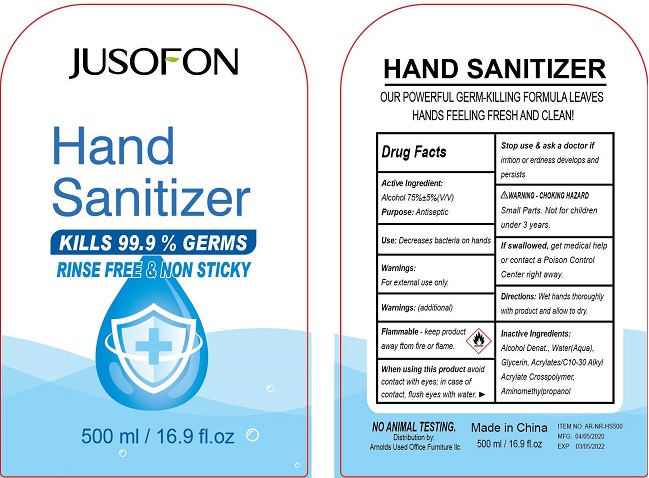 DRUG LABEL: JUSOFON Hand Sanitizer
NDC: 56136-310 | Form: GEL
Manufacturer: Ganzhou Olivee Cosmetic Co., Ltd.
Category: otc | Type: HUMAN OTC DRUG LABEL
Date: 20200430

ACTIVE INGREDIENTS: ALCOHOL 75 mL/100 mL
INACTIVE INGREDIENTS: WATER; CARBOMER INTERPOLYMER TYPE A (ALLYL SUCROSE CROSSLINKED); AMINOMETHYLPROPANOL; CARBOMER COPOLYMER TYPE A; .ALPHA.-TOCOPHEROL ACETATE, DL-; GLYCERIN

OPALINE HAND SANITIZER

Active ingredient

Alcohol 75% ±5%(V/V)

Purpose

Antiseptic

Use

Decrease bacteria on hands.

Warnings

For external use only.

Flammable.Keep product away from fire or flame.

Stop use and ask a doctor if

irritation or redness develops and persists.

Warning-Choking Hazard

Small parts, not for children under 3 years.

Keep out of reach of children.

If swallowed, get medical help or contact a Poison Control Center right away.

Small Parts. Not for children under 3 years.

Directions

Wet hands thoroughly with product and allow to dry.

Inactive ingredients

Alcohol Denat, Water (Aqua), Glycerin, Acrylates/C10-30 Alkyl Acrylate Crosspolymer, Aminomethyl Propanol